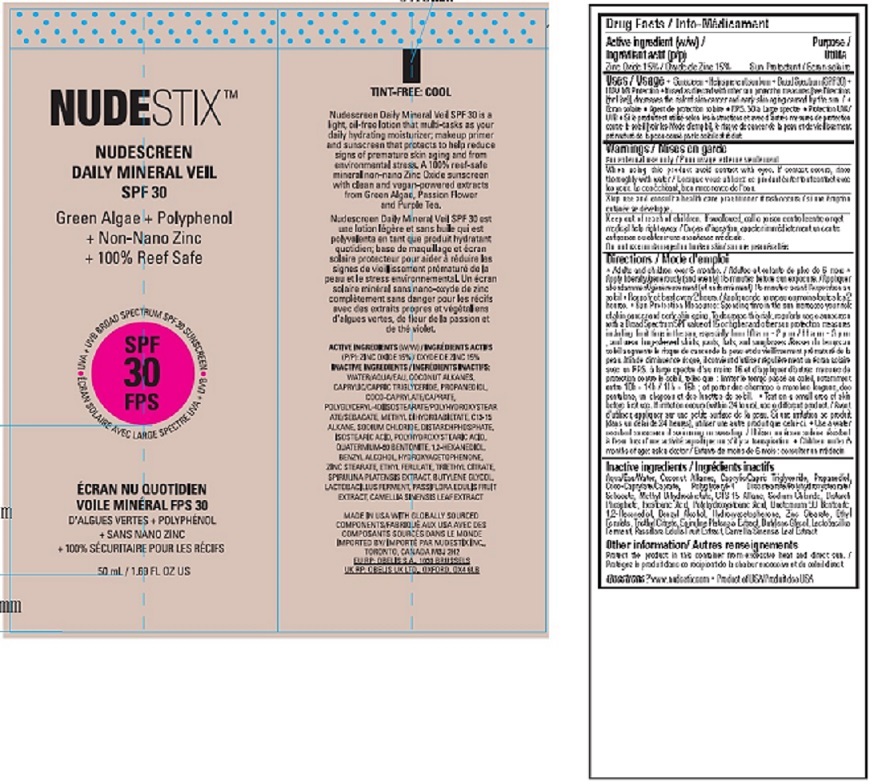 DRUG LABEL: Nudestix Daily Mineral Veil SPF 30
NDC: 54111-159 | Form: LOTION
Manufacturer: Bentley Laboratories, LLC
Category: otc | Type: HUMAN OTC DRUG LABEL
Date: 20231219

ACTIVE INGREDIENTS: ZINC OXIDE 15 g/100 mL
INACTIVE INGREDIENTS: WATER; COCONUT ALKANES; MEDIUM-CHAIN TRIGLYCERIDES; PROPANEDIOL; COCO-CAPRYLATE/CAPRATE; POLYGLYCERYL-4 DIISOSTEARATE/POLYHYDROXYSTEARATE/SEBACATE; METHYL DIHYDROABIETATE; C13-15 ALKANE; SODIUM CHLORIDE; DISTARCH PHOSPHATE, RICE; ISOSTEARIC ACID; POLYHYDROXYSTEARIC ACID (2300 MW); QUATERNIUM-90 BENTONITE; 1,2-HEXANEDIOL; BENZYL ALCOHOL; HYDROXYACETOPHENONE; ZINC STEARATE; ETHYL FERULATE; TRIETHYL CITRATE; SPIRULINA PLATENSIS; BUTYLENE GLYCOL; LACTOBACILLUS FERMENTUM; PASSIFLORA EDULIS FRUIT; GREEN TEA LEAF

Nudestix Daily Mineral Veil SPF 30 Tint-Free: Cool

ACTIVE INGREDIENT

Drug Facts / Info-Médicament

Active ingredient (w/w) / Ingrédient actif (p/p)

Zinc Oxide 15%

Purpose / Utilite

Sun Protectant

INDICATIONS AND USAGE

Uses / Usage • Sunscreen • Helps prevent sunburn • Broad Spectrum (SPF 30) •

UVA/UVB Protection • If used as directed with other sun protection measures [see Directions

(for Use)], decreases the risk of skin cancer and early skin aging caused by the sun. / •

Écran solaire • Agent de protection solaire • F.P.S. 30 à Large spectre • Protection UVA/

UVB • Si le produit est utilisé selon les instructions et avec d’autres mesures de protection

contre le soleil [voir les Mode d’emploi], le risque de cancer de la peau et de vieillissement

prématuré de la peau causé par le soleil est réduit.

Warnings / Mises en garde
For external use only / Pour usage externe seulement

When using this product avoid contact with eyes. If contact occurs, rinse

thoroughly with water. / Lorsque vous utilisez ce produit éviter tout contact avec

les yeux. Le cas échéant, bien rincer avec de l’eau.

Stop use and consult a health care practitioner if rash occurs. / si une éruption

cutanée se développe.

Keep out of reach of children. If swallowed, call a poison control centre or get

medical help right away. / En cas d’ingestion, appeler immédiatement un centre

antipoison ou obtenir une assistance médicale.

Do not use on damaged or broken skin/ sur une peau éraflée

DOSAGE AND ADMINISTRATION

Directions / Mode d’emploi
• Adults and children over 6 months. / Adultes et enfants de plus de 6 mois •

Apply liberally/generously (and evenly) 15 minutes before sun exposure. / Appliquer

abondamment/généreusement (et uniformément) 15 minutes avant l’exposition au

soleil • Reapply at least every 2 hours. / Appliquer de nouveau au moins toutes les 2

heures. • Sun Protection Measures: Spending time in the sun increases your risk

of skin cancer and early skin aging. To decrease this risk, regularly use a sunscreen

with a Broad Spectrum SPF value of 15 or higher and other sun protection measures

including: limit time in the sun, especially from 10 a.m. - 2 p.m. / 11 a.m. - 3 p.m.

; and wear long-sleeved shirts, pants, hats, and sunglasses /Passer du temps au

soleil augmente le risque de cancer de la peau et du vieillissement prématuré de la

peau. Afin de diminuer ce risque, il convient d’utiliser régulièrement un écran solaire

avec un F.P.S. à large spectre d’au moins 15 et d’appliquer d’autres mesures de

protection contre le soleil, telles que : limiter le temps passé au soleil, notamment

entre 10h - 14h / 11h - 15h ; et porter des chemises à manches longues, des

pantalons, un chapeau et des lunettes de soleil. • Test on a small area of skin

before first use. If irritation occurs (within 24 hours), use a different product. / Avant

d’utiliser, appliquer sur une petite surface de la peau. Si une irritation se produit

(dans un délai de 24 heures), utiliser une autre produit que celui-ci. • Use a water

resistant sunscreen if swimming or sweating. / Utiliser un écran solaire résistant

à l’eau lors d’une activité aquatique ou s’il y a transpiration. • Children under 6

months of age: ask a doctor / Enfants de moins de 6 mois : consulter un médecin

Inactive ingredients / Ingrédients inactifs
Aqua/Eau/Water, Coconut Alkanes, Caprylic/Capric Triglyceride, Propanediol,

Coco-Caprylate/Caprate, Polyglyceryl-4 Diisostearate/Polyhydroxystearate/

Sebacate, Methyl Dihydroabietate, C13-15 Alkane, Sodium Chloride, Distarch

Phosphate, Isostearic Acid, Polyhydroxystearic Acid, Quaternium-90 Bentonite,

1,2-Hexanediol, Benzyl Alcohol, Hydroxyacetophenone, Zinc Stearate, Ethyl

Ferulate, Triethyl Citrate, Spirulina Platensis Extract, Butylene Glycol, Lactobacillus

Ferment, Passiflora Edulis Fruit Extract, Camellia Sinensis Leaf Extract

Other information/ Autres renseignements
Protect the product in this container from excessive heat and direct sun. /

Protégez le produit dans ce récipient de la chaleur excessive et du soleil direct.

QUESTIONS

Questions?www.nudestix.com • Product of USA/Produit des USA

Principal Display Package - NUDESTIX™ DAILY MINERAL VEIL SPF 30 TINT-FREE: COOL

NUDESTIX™

NUDESCREEN

DAILY MINERAL VEIL

SPF 30

50 mL / 1.69 FL OZ US

TINT-FREE: COOL

MADE IN USA WITH GLOBALLY SOURCED COMPONENTS

IMPORTED BY NUDESTIX INC.

res